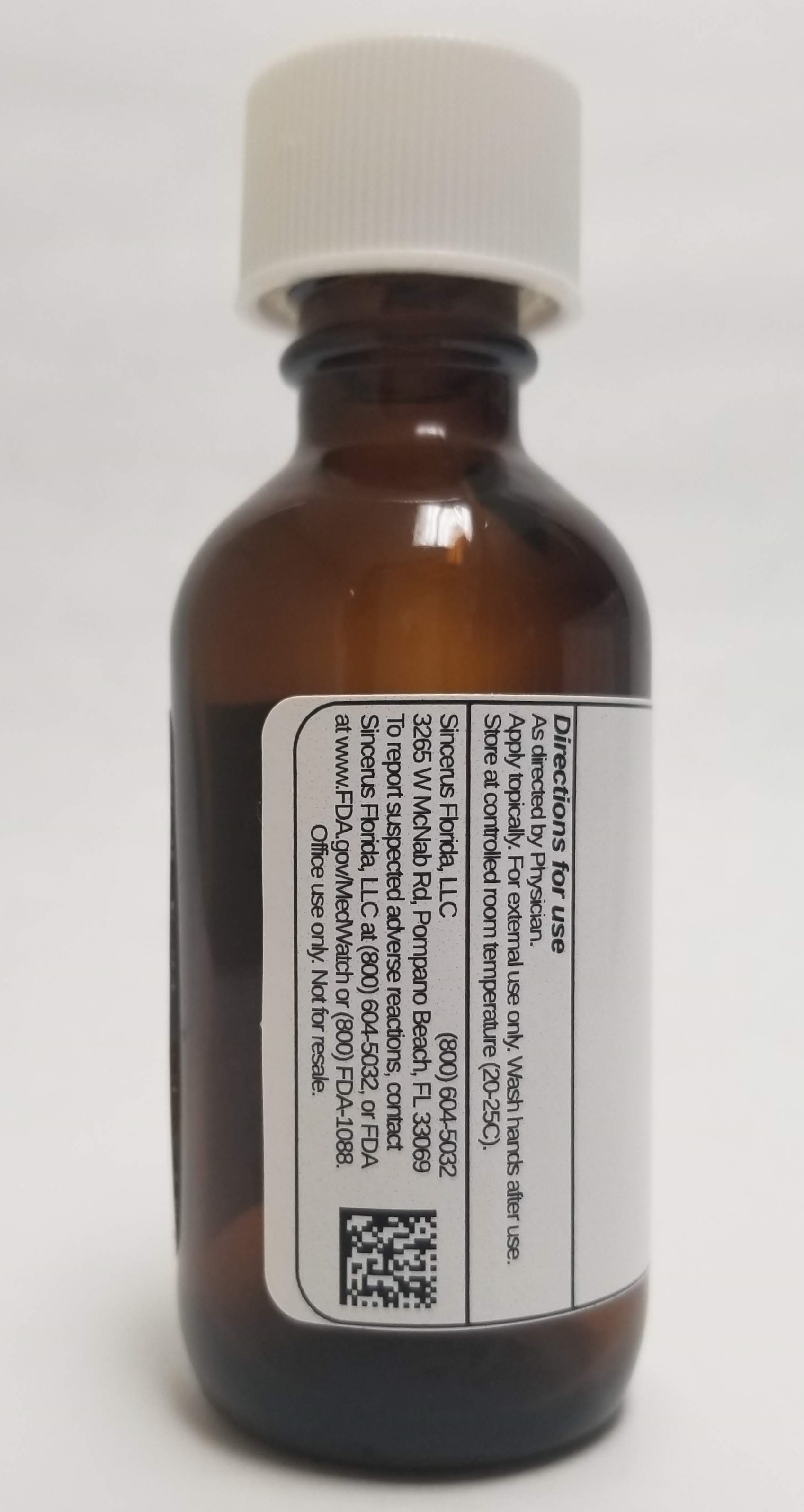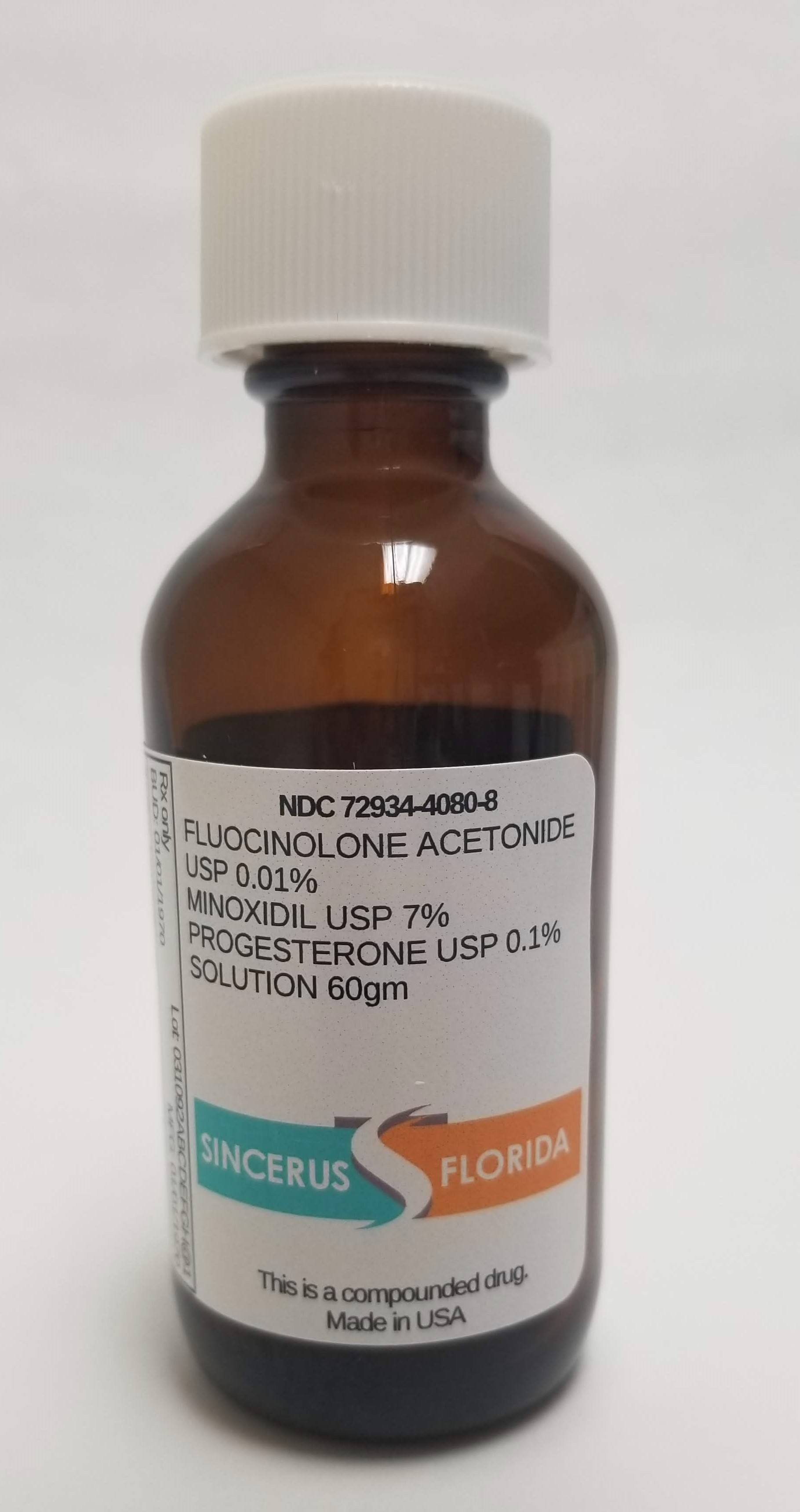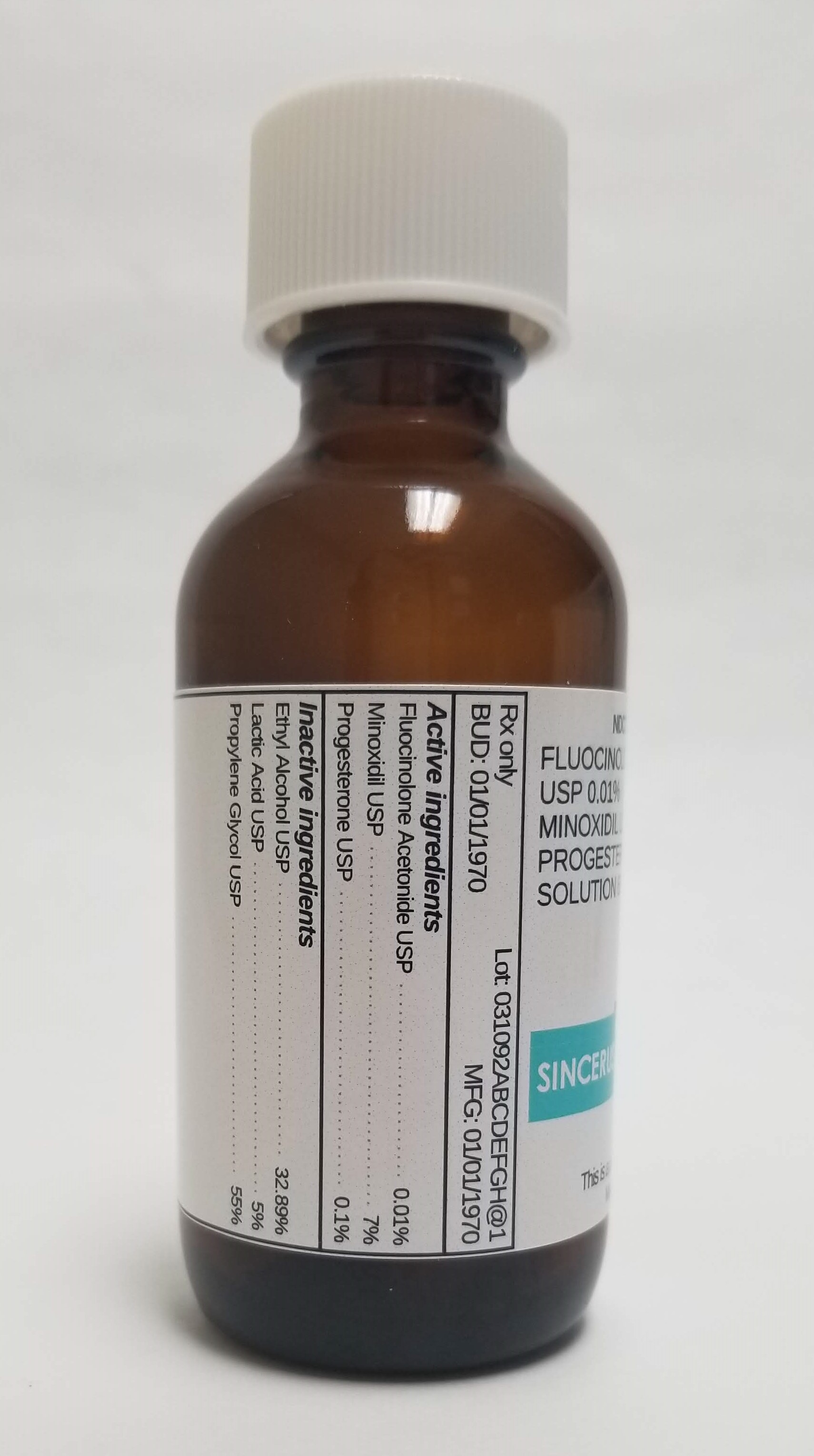 DRUG LABEL: FLUOCINOLONE ACETONIDE 0.01% / MINOXIDIL 7% / PROGESTERONE 0.1%
NDC: 72934-4080 | Form: SOLUTION
Manufacturer: Sincerus florida, LLC
Category: prescription | Type: HUMAN PRESCRIPTION DRUG LABEL
Date: 20190508

ACTIVE INGREDIENTS: FLUOCINOLONE ACETONIDE 0.01 g/100 g; MINOXIDIL 7 g/100 g; PROGESTERONE 0.1 g/100 g

FLUOCINOLONE ACETONIDE 0.01% / MINOXIDIL 7% / PROGESTERONE 0.1%